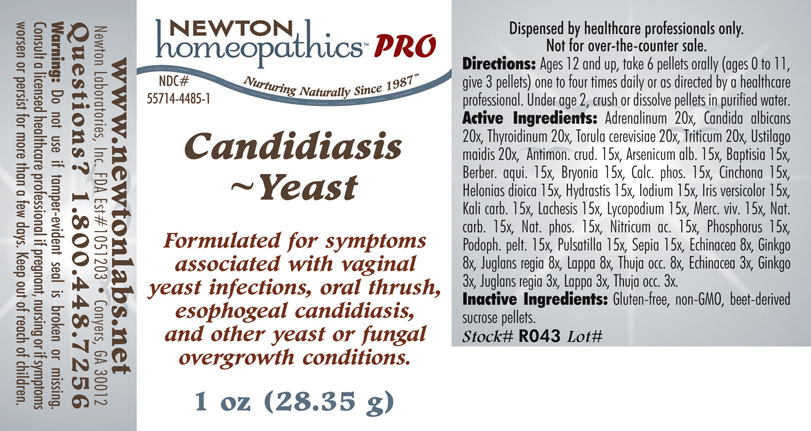 DRUG LABEL: Candidiasis - Yeast 
NDC: 55714-4485 | Form: PELLET
Manufacturer: Newton Laboratories, Inc.
Category: homeopathic | Type: HUMAN PRESCRIPTION DRUG LABEL
Date: 20110601

ACTIVE INGREDIENTS: Epinephrine 20 [hp_X]/1 g; Candida Albicans 20 [hp_X]/1 g; Thyroid, Unspecified 20 [hp_X]/1 g; Saccharomyces Cerevisiae 20 [hp_X]/1 g; Elymus Repens Root 20 [hp_X]/1 g; Ustilago Maydis 20 [hp_X]/1 g; Antimony Trisulfide 15 [hp_X]/1 g; Arsenic Trioxide 15 [hp_X]/1 g; Baptisia Tinctoria Root 15 [hp_X]/1 g; Mahonia Aquifolium Root Bark 15 [hp_X]/1 g; Bryonia Alba Root 15 [hp_X]/1 g; Tribasic Calcium Phosphate 15 [hp_X]/1 g; Cinchona Officinalis Bark 15 [hp_X]/1 g; Chamaelirium Luteum Root 15 [hp_X]/1 g; Goldenseal 15 [hp_X]/1 g; Iodine 15 [hp_X]/1 g; Iris Versicolor Root 15 [hp_X]/1 g; Potassium Carbonate 15 [hp_X]/1 g; Lachesis Muta Venom 15 [hp_X]/1 g; Lycopodium Clavatum Spore 15 [hp_X]/1 g; Mercury 15 [hp_X]/1 g; Sodium Carbonate 15 [hp_X]/1 g; Sodium Phosphate, Dibasic, Heptahydrate 15 [hp_X]/1 g; Nitric Acid 15 [hp_X]/1 g; Phosphorus 15 [hp_X]/1 g; Podophyllum 15 [hp_X]/1 g; Pulsatilla Vulgaris 15 [hp_X]/1 g; Sepia Officinalis Juice 15 [hp_X]/1 g; Echinacea, Unspecified 8 [hp_X]/1 g; Ginkgo 8 [hp_X]/1 g; English Walnut 8 [hp_X]/1 g; Arctium Lappa Root 8 [hp_X]/1 g; Thuja Occidentalis Leafy Twig 8 [hp_X]/1 g
INACTIVE INGREDIENTS: Sucrose

Candidiasis - Yeast

INDICATIONS & USAGE SECTION

Candida - Yeast Formulated for symptoms associated with vaginal yeast infections, oral thrush, esophogeal candidiasis, and other yeast or fungal overgrowth conditions.

DOSAGE & ADMINISTRATION SECTION

Directions: Ages 12 and up, take 6 pellets orally (ages 0 to 11, give 3 pellets) one to four times daily or as directed by a healthcare professional. Under age 2, crush or dissolve pellets in purified water.

ACTIVE INGREDIENT SECTION

Adrenalinum 20x, Candida albicans 20x, Thyroidinum 20x, Torula cerevisiae 20x, Triticum 20x, Ustilago maidis 20x, Antimon. crud. 15x, Arsenicum alb. 15x, Baptisia 15x, Berber. aqui. 15x, Bryonia 15x, Calc. phos. 15x, Cinchona 15x, Helonias dioica 15x, Hydrastis 15x, Iodium 15x, Iris versicolor 15x, Kali carb. 15x, Lachesis 15x, Lycopodium 15x, Merc. viv. 15x, Nat. carb. 15x, Nat. phos. 15x, Nitricum ac. 15x, Phosphorus 15x, Podoph. pelt. 15x, Pulsatilla 15x, Sepia 15x, Echinacea 8x, Ginkgo 8x, Juglans regia 8x, Lappa 8x, Thuja occ. 8x, Echinacea 3x, Ginkgo 3x, Juglans regia 3x, Lappa 3x, Thuja occ. 3x.

PURPOSE SECTION

Formulated for symptoms associated with vaginal yeast infections, oral thrush, esophogeal candidiasis, and other yeast or fungal overgrowth conditions.

INACTIVE INGREDIENT SECTION

Gluten-free, non-GMO, beet-derived sucrose pellets.

QUESTIONS? SECTION

www.newtonlabs.net Newton Laboratories, Inc. FDA Est # 1051203 - Conyers, GA 30012
Questions? 1.800.448.7256

WARNINGS SECTION

Warning: Do not use if tamper - evident seal is broken or missing. Consult a licensed healthcare professional if pregnant, nursing or if symptoms worsen or persist for more than a few days. Keep out of reach of children.

PREGNANCY OR BREAST FEEDING SECTION

Consult a licensed healthcare professional if pregnant or nursing or if symptoms worsen or persist for more than a few days.

KEEP OUT OF REACH OF CHILDREN SECTION

Keep out of reach of children.